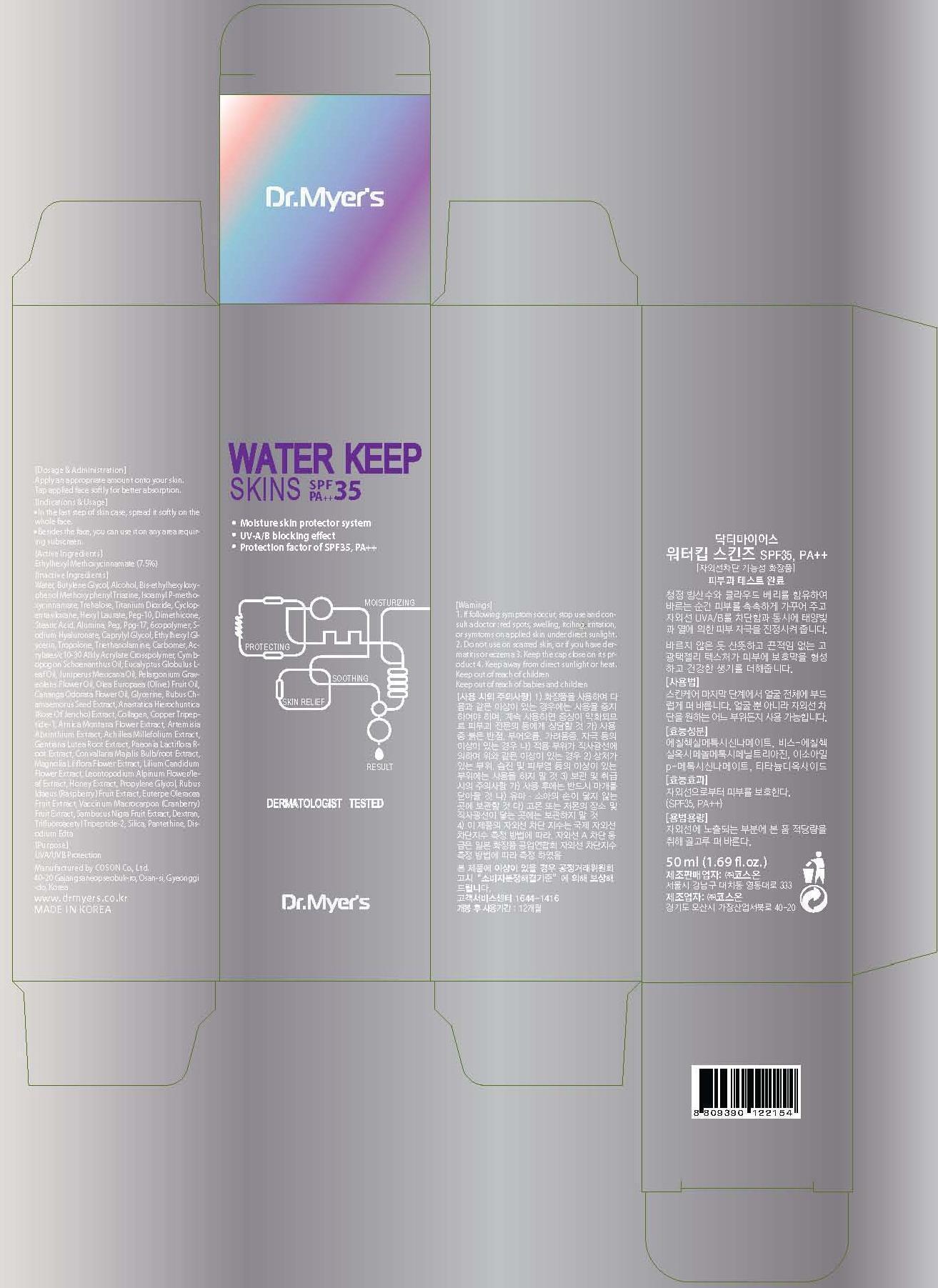 DRUG LABEL: DR MYERS WATER KEEP SKINS
NDC: 62171-010 | Form: CREAM
Manufacturer: Coson Co., Ltd.
Category: otc | Type: HUMAN OTC DRUG LABEL
Date: 20140214

ACTIVE INGREDIENTS: OCTINOXATE 3.75 mg/50 mL
INACTIVE INGREDIENTS: WATER; BUTYLENE GLYCOL

ACTIVE INGREDIENT

Active Ingredient: ETHYLHEXYL METHOXYCINNAMATE 7.5%

INACTIVE INGREDIENT

Inactive Ingredients:
WATER, BUTYLENE GLYCOL, ALCOHOL, BIS-ETHYLHEXYLOXYPHENOL METHOXYPHENYL TRIAZINE, ISOAMYL p-METHOXYCINNAMATE, TREHALOSE, TITANIUM DIOXIDE, CYCLOPENTASILOXANE, HEXYL LAURATE, PEG-10, DIMETHICONE, STEARIC ACID, ALUMINA, PEG, PPG-17, 6COPOLYMER, SODIUM HYALURONATE, CAPRYLYL GLYCOL, ETHYLHEXYL GLYCERIN, TROPOLONE, TRIETHANOLAMINE, CARBOMER, ACRYLATES/C10-30 ALKLY ACRYLATE CROSSPOLYMER, CYMBOPOGON SCHOENANTHUS OIL, EUCALYPTUS GLOBULUS LEAF OIL, JUNIPERUS MEXICANA OIL, PELARGONIUM GRAVEOLENS FLOWER OIL, OLEA EUROPAEA (OLIVE) FRUIT OIL, CANANGA ODORATA FLOWER OIL, GLYCERINE, RUBUS CHAMAEMORUS SEED EXTRACT, ANASTATICA HIEROCHUNTICA (ROSE OF JERICHO) EXTRACT, COLLAGEN, COPPER TRIPEPTIDE-1, ARNICA MONTANA FLOWER EXTRACT, ARTEMISIA ABSINTHIUM EXTRACT, ACHILLEA MILLEFOLIUM EXTRACT, GENTIANA LUTEA ROOT EXTRACT, PAEONIA LACTIFLORA ROOT EXTRACT, CONVALLARIA MAJALIS BULB/ROOT EXTRACT, MAGNOLIA LILIFLORA FLOWER EXTRACT, LILIUM CANDIDUM FLOWER EXTRACT, LEONTOPODIUM ALPINUM FLOWER/LEAF EXTRACT, HONEY EXTRACT, PROPYLENE GLYCOL, RUBUS IDAEUS (RASPBERRY) FRUIT EXTRACT, EUTERPE OLERACEA FRUIT EXTRACT, VACCINUM MACROCARPON (CRANBERRY) FRUIT EXTRACT, SAMBUCUS NIGRA FRUIT EXTRACT, DEXTRAN, TRIFLUOROACETYL TRIPEPTIDE-2, SILICA, PANTETHINE, DISODIUM EDTA

PURPOSE

PURPOSE: UVA/UVB Protection

WARNINGS

1. If following symptoms occur, stop use and consult a doctor : red spots, swelling, itcihng, irritation, or symtoms on applied skin under direct sunlight.
2. Do not use on scarred skin, or if you have dermatitis or eczema
3. Keep the cap close on its product
4. Keep away from direct sunlight or heat.

KEEP OUT OF REACH OF CHILDREN

Keep out of reach of babies and children

INDICATIONS AND USAGE

In the last step of skin care, spread it softly on the whole face.
Beside the face, you can use it on any area if you think sunscreen needed.

DOSAGE AND ADMINISTRATION

Apply an appropriate amount onto your skin. Tap applied face softly for better absorption.